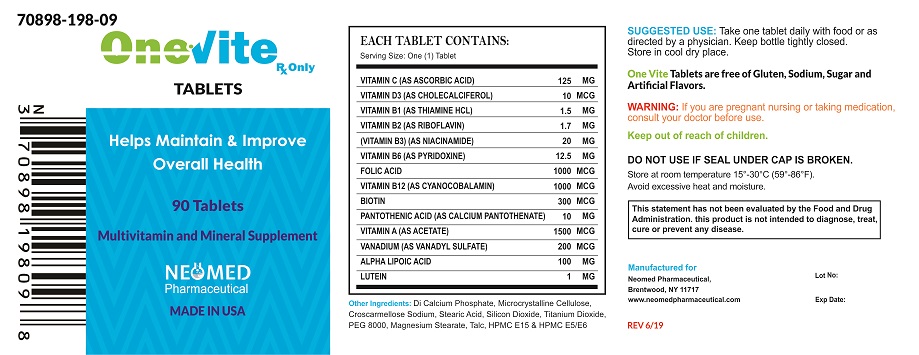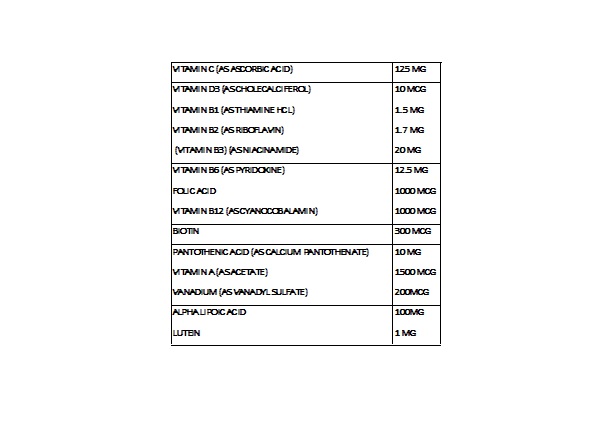 DRUG LABEL: ONEvite
NDC: 70898-198 | Form: TABLET
Manufacturer: NEOMED PHARMACEUTICAL
Category: other | Type: DIETARY SUPPLEMENT
Date: 20190614

ACTIVE INGREDIENTS: ASCORBIC ACID 125 mg/1 1; CHOLECALCIFEROL 10 ug/1 1; THIAMINE HYDROCHLORIDE 1.5 mg/1 1; RIBOFLAVIN 1.7 mg/1 1; NIACINAMIDE 20 mg/1 1; PYRIDOXINE 12.5 mg/1 1; FOLIC ACID 1000 ug/1 1; CYANOCOBALAMIN 1000 ug/1 1; BIOTIN 300 ug/1 1; CALCIUM PANTOTHENATE 10 mg/1 1; VITAMIN A ACETATE 1500 ug/1 1; VANADYL SULFATE 200 ug/1 1; .ALPHA.-LIPOIC ACID 100 mg/1 1; LUTEIN 1 mg/1 1
INACTIVE INGREDIENTS: CALCIUM PHOSPHATE, DIBASIC, ANHYDROUS; MICROCRYSTALLINE CELLULOSE; CROSCARMELLOSE SODIUM; STEARIC ACID; SILICON DIOXIDE; TITANIUM DIOXIDE; POLYETHYLENE GLYCOL 8000; MAGNESIUM STEARATE; TALC; HYPROMELLOSES

Multivitamin and Mineral Supplement
Rx only

STATEMENT OF IDENTITY

Each Tablet Contains:

Other Ingredients: Di calcium phosphate, microcrystalline cellulose, croscarmellose sodium, stearic acid, silicon dioxide, titanium dioxide, PEG 8000, magnesium stearate, talc, HPMC E15 & HPMC E5/E6

WARNINGS

INDICATIONS AND USAGE

ONEvite Tablets is an orally administered prescription vitamin supplement specifically formulated for the clinical dietary management of patients with unique nutritional needs requiring, increased folate levels and nutritional supplementation in physiologically stressful conditions. As well as for maintenance of good health and beneficial in maintaining overall skin health, also help maintain healthy blood sugar levels and help promote nerve health and function including normal vision.

CONTRAINDICATIONS

ONEvite Tablets is contraindicated in patients with hypersensitivity to any of its components. Folic Acid is contraindicated in patients with untreated and uncomplicated pernicious anemia, and in those with anaphylactic sensitivity to folic acid.

Cyanocobalamin is contraindicated in patients with sensitivity to cobalt or to cyanocobalamin (Vitamin B12).

WARNING/PRECAUTIONS

Vitamin D supplementation should be used with caution in those with hypercalcemia or conditions that may lead to hypercalcemia such as hyperparathyroidism and those who form calcium-containing kidney stones. High doses of vitamin D can lead to elevated levels of calcium that reside in the blood and soft tissues. Bone pain, high blood pressure, formation of kidney stones, renal failure, and increased risk of heart disease can occur.

Folic acid, especially in doses above 0.1 mg daily, may obscure pernicious anemia, in that hematologic remission may occur while neurological manifestations remain progressive.

The use of folic acid doses above 1 mg daily may precipitate or exacerbate the neurological damage of vitamin B12 deficiency.

Avoid Over dosage. Keep out of the reach of children.

Drug Interactions

High doses of folic acid may result in decreased serum levels of anticonvulsant drugs.

Vitamin D supplementation should not be given with large amounts of calcium in those with hypercalcemia or conditions that may lead to hypercalcemia such as hyperparathyroidism and those who form calcium-containing kidney stones.

Consult appropriate references for additional specific vitamin-drug interactions.

Information for Patients

Patients should be counseled to disclose all medical conditions, including use of all medications, vitamins and supplements, pregnancy, and breastfeeding.

Pediatric Use

Not recommended for pediatric use.

ADVERSE REACTIONS

Adverse reactions have been reported with specific vitamins and minerals, but generally at levels substantially higher than those in ONEvite Tablets

DOSAGE AND ADMINISTRATION

ONEvite Tablets is a white film coating with caplet shape.

One tablet daily or as directed by a physician.

HEALTH CLAIM

HOW SUPPLIED

ONEvite Tablets available 90 tablets per bottle,

70898-198-09

Store at room temperature 15°-30°C (59°-86°F). Avoid excessive heat and moisture.

To report a serious adverse event or obtain product information, call 631-524-5758

Manufactured for:

Neomed Pharmaceutical

Brentwood, NY 11717

www.neomedpharmaceutical.com

MADE IN USA

DISCLAIMER: This drug has not been found by FDA to be safe and effective, and this labeling has not been approved by FDA. For further information about unapproved drugs, click here.